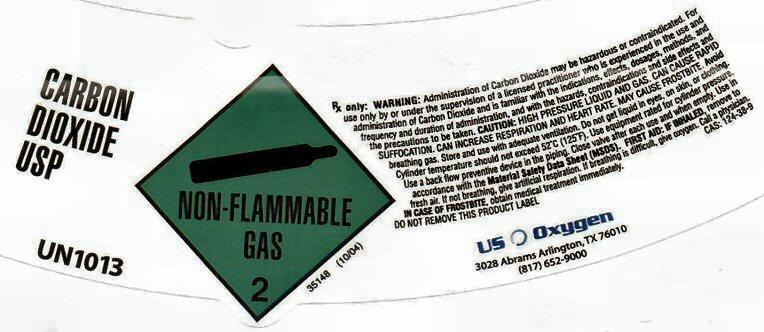 DRUG LABEL: CARBON DIOXIDE
NDC: 54632-004 | Form: GAS
Manufacturer: U.S. Oxygen and Supply, LLC
Category: prescription | Type: HUMAN PRESCRIPTION DRUG LABEL
Date: 20140221

ACTIVE INGREDIENTS: CARBON DIOXIDE 99 L/100 L

CARBON DIOXIDE USP SL

CARBON DIOXIDE USP UN103 NON-FLAMMABLE GAS 2

35148 (10/04)

Rx only. WARNING: Administration of Carbon Dioxide may be hazardous or contraindicated. For use only by or under the supervision of a licensed practitioner who is experienced in the use and administration of Carbon Dioxide and is familiar with the indications, effects, dosages, methods, and frequency and duration of administration, and with the hazards, contraindications and side effects and the precautions to be taken.CAUTION: FEDERAL LAW PROHIBITS DISPENSING WITHOUT PRESCRIPTION
CAUTION: HIGH PRESSURE LIQUID AND GAS. CAN CAUSE RAPID SUFFOCATION (DUE TO OXYGEN DEFICIENCY). CAN INCREASE RESPIRATIONS AND HEART RATE. MAY CAUSE FROSTBITE. Avoid breathing gas. Store and use with adequate ventilation. Do not get liquid in eyes, on skin, or clothing. Cylinder temperature should not exceed 125° F (52° C). Use equipment rated for cylinder pressure. Use a back flow preventive device in the piping. Close valve after each use and when empty. Use in accordance with the Material Safety Data Sheet (MSDS). FIRST AID: IF INHALED, remove to fresh air. If not breathing, give artificial respiration. If breathing is difficult, give oxygen. Call a physician. IN CASE OF FROSTBITE, obtain medical treatment immediately.

DO NO REMOVE THIS LABEL CAS: 124-38-9

US Oxygen
3028 Abrams Arlington TX 76010 (817) 652-9000